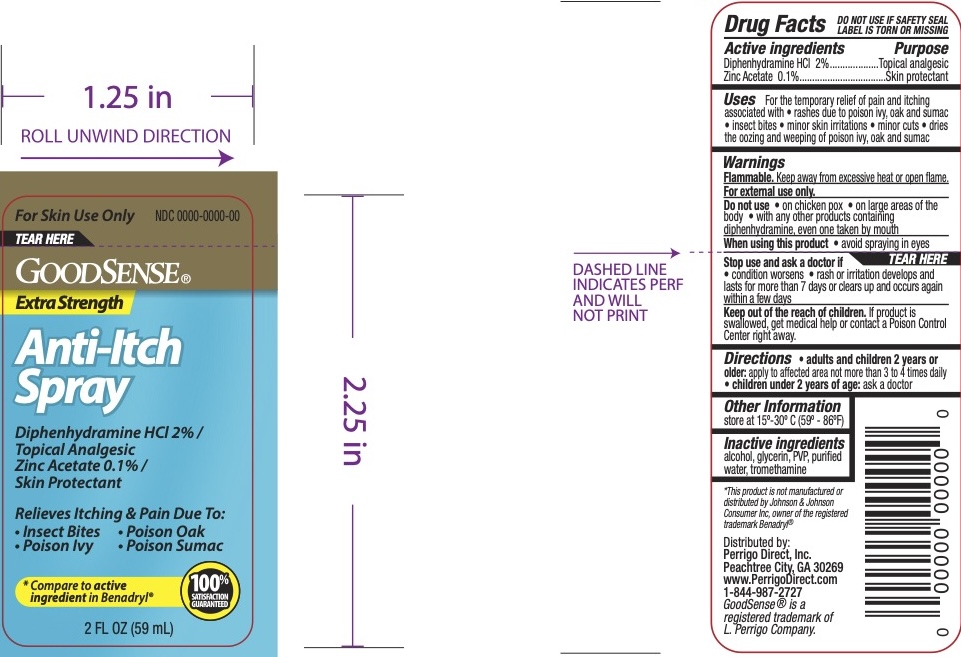 DRUG LABEL: GoodSense Anti-Itch
NDC: 50804-064 | Form: SPRAY
Manufacturer: Geiss, Destin & Dunn, Inc
Category: otc | Type: HUMAN OTC DRUG LABEL
Date: 20250228

ACTIVE INGREDIENTS: DIPHENHYDRAMINE HYDROCHLORIDE 2 g/100 mL; ZINC ACETATE 0.1 g/100 mL
INACTIVE INGREDIENTS: WATER; ALCOHOL; GLYCERIN; PVP; TROMETHAMINE

GoodSense Anti-Itch Spray

ACTIVE INGREDIENT

Diphenhydramine HCl 2%, Zinc Acetate 0.1%

PURPOSE

Topical Analgesic, Skin Protectant

INDICATIONS AND USAGE

For the temporary relief of pain and itching associated with rashes due to poison ivy, oak and sumac, insect bites, minor skin irritations, minor cuts, dries the oozing and weeping of poison ivy, oak and sumac.

WARNINGS

Flammable. Keep away from excessive heat or open flame.

For external use only.

Do not use on chicken pox, on large areas of the body, with any other products containing diphenhydramine, even one take by mouth.

When using this product avoid spraying in eyes.

Stop use and ask a doctor if the condition worsens, rash or irritation develops and lasts for more than 7 days or clears up and occurs again within a few days.

Keep out of reach of children. If the product is swallowed, get medical help or contact a Poison Control Center right away.

DOSAGE AND ADMINISTRATION

Adults and children 2 years or older: apply to affected area not more than 3 to 4 times daily. Children under 2 years of age: ask a doctor.

INACTIVE INGREDIENT

Blue 1, carbomer, isopropyl alcohol, magnesium sulfate, sodium hydroxide, water, and yellow 5.